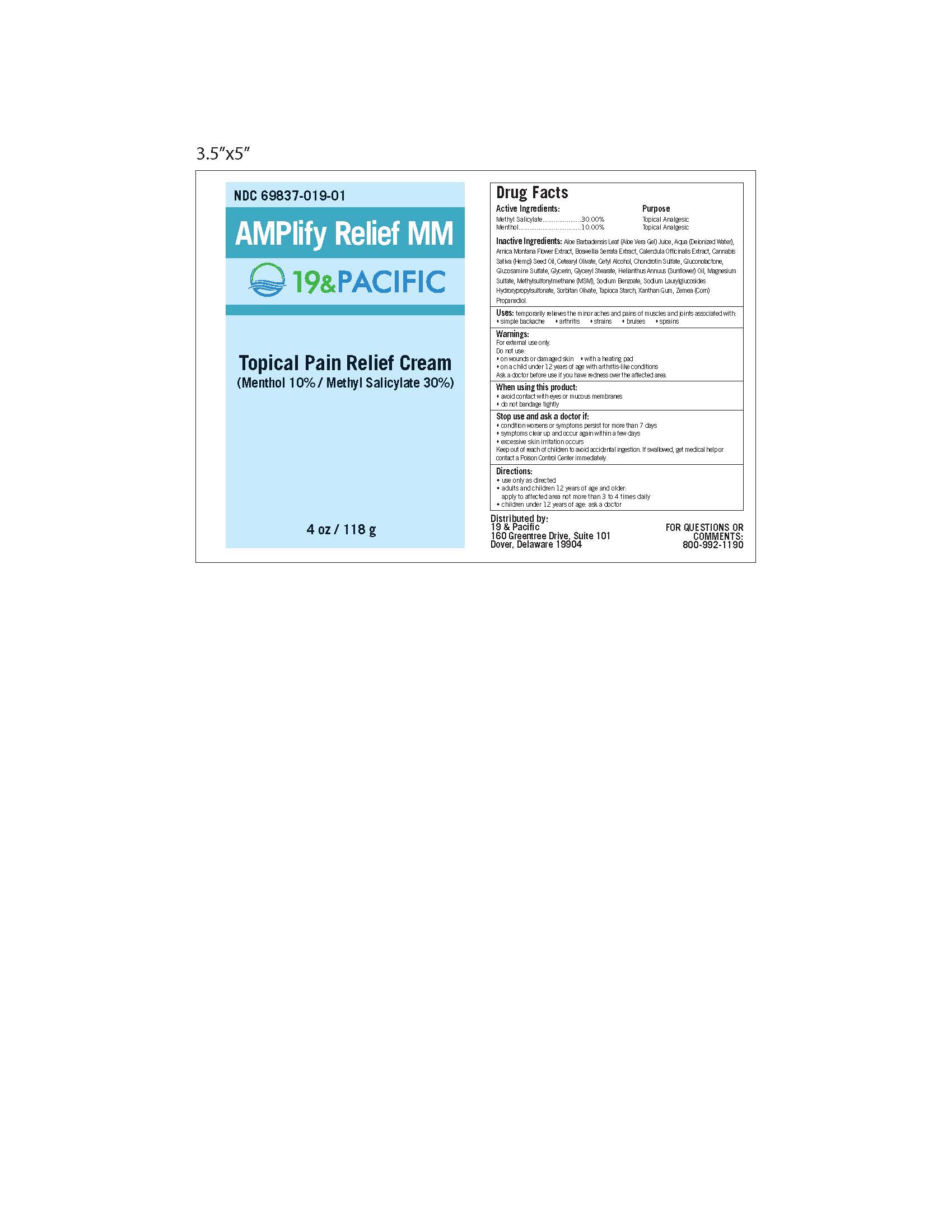 DRUG LABEL: AMPlify Relief MM
NDC: 69837-019 | Form: CREAM
Manufacturer: International Brand Management, LLC
Category: otc | Type: HUMAN OTC DRUG LABEL
Date: 20170313

ACTIVE INGREDIENTS: METHYL SALICYLATE 3 g/10 g; MENTHOL 1 g/10 g
INACTIVE INGREDIENTS: ALOE VERA LEAF; WATER; ARNICA MONTANA FLOWER; INDIAN FRANKINCENSE; CALENDULA OFFICINALIS FLOWER; CANNABIS SATIVA SEED OIL; Cetearyl Olivate; CETYL ALCOHOL; CHONDROITIN SULFATE (SHARK); GLUCONOLACTONE; Glucosamine Sulfate; GLYCERIN; GLYCERYL STEARATE SE; SUNFLOWER OIL; MAGNESIUM SULFATE, UNSPECIFIED FORM; DIMETHYL SULFONE; SODIUM BENZOATE; SORBITAN OLIVATE; STARCH, TAPIOCA; XANTHAN GUM; PROPANEDIOL

Active Ingredients:

Methyl Salicylate....30.00%

Menthol.................10.00%

Purpose

Topical Analgesic

Topical Analgesic

INDICATIONS AND USAGE

Uses: temporarily relieves the minor aches and pains of muscles and joints associated with:

-simple backache -arthritis -strains -bruises -sprains

Warnings:

For external use only

Do not use:

-on wounds or damaged skin -with a heating pad

-on a child under 12 years of age with arthritis-like conditions

Ask a doctor before use if you have redness over the affected area

When using this product:

-avoid contact with eyes or mucous membranes

-do not bandage tightly

Stop use and ask a doctor if:

-condition worsens or symptoms persist for more than 7 days

-symptoms clear up and occur again within a few days

-excessive skin irritation occurs

Keep out of reach of children to avoid accidental ingestion. If swallowed, get medical help or

contact a Poison Control Center immediately

Directions:

-use only as directed

-adults and children 12 years of age and older:

apply to affected area not more than 3 to 4 times daily

-children under 12 years of age: ask a doctor

INACTIVE INGREDIENT

Inactive Ingredients: Aloe Barbadensis Leaf (Aloe Vera Gel) Juice, Aqua (Deionized Water),

Arnica Montana Flower Extract, Boswellia Serrata Extract, Calendula Officinalis Extract, Cannabis

Sativa (Hemp) Seed Oil, Cetearyl Olivate, Cetyl Alcohol, Chondrotin Sulfate, Gluconolactone,

Glucosamine Sulfate, Glycerin, Glyceryl Stearate, Helianthus Annuus (Sunflower) Oil, Magnesium

Sulfate, Methylsulfonylmethane (MSM), Sodium Benzoate, Sodium Laurylglucosides

Hydroxypropylsulfonate, Sorbitan Olivate, Tapioca Starch, Xanthan Gum, Zemea (Corn)

Propanediol.